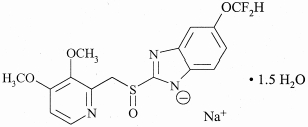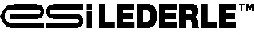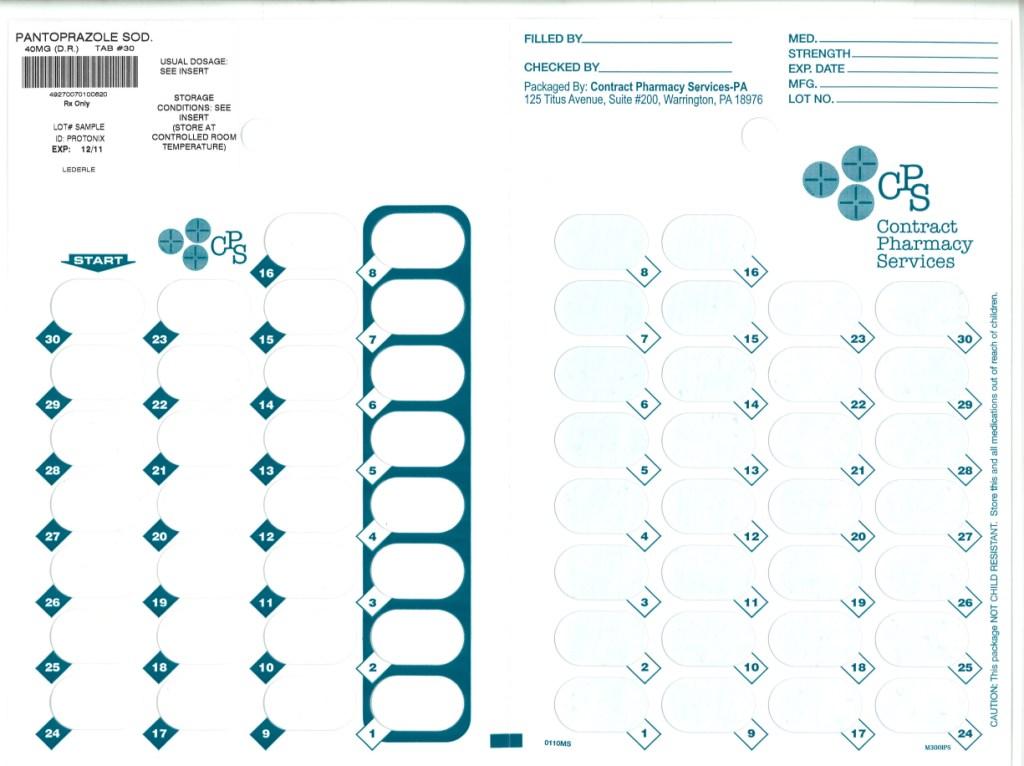 DRUG LABEL: Pantoprazole Sodium
NDC: 67046-535 | Form: TABLET, DELAYED RELEASE
Manufacturer: Contract Pharmacy Services-PA
Category: prescription | Type: HUMAN PRESCRIPTION DRUG LABEL
Date: 20090331

ACTIVE INGREDIENTS: PANTOPRAZOLE SODIUM 40 mg/1 1
INACTIVE INGREDIENTS: Calcium Stearate; Crospovidone; Hypromellose; Ferric Oxide Yellow; Mannitol; Polysorbate 80; Povidone; Propylene Glycol; Sodium Carbonate; Sodium Lauryl Sulfate; Titanium Dioxide; Triethyl Citrate; METHACRYLIC ACID - ETHYL ACRYLATE COPOLYMER (1:1) TYPE A

Pantoprazole Sodium
Delayed-Release Tablets

Rx only

DESCRIPTION

The active ingredient in pantoprazole sodium delayed-release tablets is a substituted benzimidazole, sodium 5-(difluoromethoxy)-2-[[(3,4-dimethoxy-2-pyridinyl)methyl] sulfinyl]-1H-benzimidazole sesquihydrate, a compound that inhibits gastric acid secretion. Its empirical formula is C16H14F2N3NaO4S x 1.5 H2O, with a molecular weight of 432.4. The structural formula is:

Pantoprazole sodium sesquihydrate is a white to off-white crystalline powder and is racemic. Pantoprazole has weakly basic and acidic properties. Pantoprazole sodium sesquihydrate is freely soluble in water, very slightly soluble in phosphate buffer at pH 7.4, and practically insoluble in n‑hexane.

The stability of the compound in aqueous solution is pH-dependent. The rate of degradation increases with decreasing pH. At ambient temperature, the degradation half-life is approximately 2.8 hours at pH 5.0 and approximately 220 hours at pH 7.8.

Pantoprazole sodium is supplied as a delayed-release tablet for oral administration, available in 2 strengths. Each delayed-release tablet contains 45.1 mg or 22.6 mg of pantoprazole sodium sesquihydrate (equivalent to 40 mg or 20 mg pantoprazole, respectively) with the following inactive ingredients: calcium stearate, crospovidone, hypromellose, iron oxide, mannitol, methacrylic acid copolymer, polysorbate 80, povidone, propylene glycol, sodium carbonate, sodium lauryl sulfate, titanium dioxide, and triethyl citrate. Pantoprazole Sodium Delayed‑Release tablets (40 mg and 20 mg) complies with USP dissolution test 2.

CLINICAL PHARMACOLOGY

Pharmacokinetics

Pantoprazole sodium is prepared as an enteric-coated tablet so that absorption of pantoprazole begins only after the tablet leaves the stomach. Peak serum concentration (Cmax) and area under the serum concentration time curve (AUC) increase in a manner proportional to oral and intravenous doses from 10 mg to 80 mg. Pantoprazole does not accumulate and its pharmacokinetics are unaltered with multiple daily dosing. Following oral or intravenous administration, the serum concentration of pantoprazole declines biexponentially with a terminal elimination half-life of approximately one hour. In extensive metabolizers (see CLINICAL PHARMACOLOGY, Pharmacokinetics, Metabolism) with normal liver function receiving an oral dose of the enteric-coated 40 mg pantoprazole tablet, the peak concentration (Cmax) is 2.5 μg/mL, the time to reach the peak concentration (tmax) is 2.5 h and the total area under the plasma concentration versus time curve (AUC) is 4.8 μg·hr/mL. When pantoprazole is given with food, its tmax is highly variable and may increase significantly. Following intravenous administration of pantoprazole to extensive metabolizers, its total clearance is 7.6-14.0 L/h and its apparent volume of distribution is 11.0-23.6 L.

Absorption

The absorption of pantoprazole is rapid, with a Cmax of 2.5 μg/mL that occurs approximately 2.5 hours after administration of a single or multiple oral 40-mg doses of pantoprazole sodium delayed-release tablets. Pantoprazole is well absorbed; it undergoes little first-pass metabolism resulting in an absolute bioavailability of approximately 77%. Pantoprazole absorption is not affected by concomitant administration of antacids. Administration of pantoprazole with food may delay its absorption up to 2 hours or longer; however, the Cmax and the extent of pantoprazole absorption (AUC) are not altered. Thus, pantoprazole may be taken without regard to timing of meals.

Distribution

The apparent volume of distribution of pantoprazole is approximately 11.0-23.6 L, distributing mainly in extracellular fluid. The serum protein binding of pantoprazole is about 98%, primarily to albumin.

Metabolism

Pantoprazole is extensively metabolized in the liver through the cytochrome P450 (CYP) system. Pantoprazole metabolism is independent of the route of administration (intravenous or oral). The main metabolic pathway is demethylation, by CYP2C19, with subsequent sulfation; other metabolic pathways include oxidation by CYP3A4. There is no evidence that any of the pantoprazole metabolites have significant pharmacologic activity. CYP2C19 displays a known genetic polymorphism due to its deficiency in some sub-populations (eg, 3% of Caucasians and African-Americans and 17%-23% of Asians). Although these sub-populations of slow pantoprazole metabolizers have elimination half-life values of 3.5 to 10.0 hours, they still have minimal accumulation (≤ 23%) with once daily dosing.

Elimination

After a single oral or intravenous dose of ^14C-labeled pantoprazole to healthy, normal metabolizer volunteers, approximately 71% of the dose was excreted in the urine with 18% excreted in the feces through biliary excretion. There was no renal excretion of unchanged pantoprazole.

Special Populations

Geriatric

Only slight to moderate increases in pantoprazole AUC (43%) and Cmax (26%) were found in elderly volunteers (64 to 76 years of age) after repeated oral administration, compared with younger subjects. No dosage adjustment is recommended based on age.

Pediatric

The pharmacokinetics of pantoprazole have not been investigated in patients < 18 years of age.

Gender

There is a modest increase in pantoprazole AUC and Cmax in women compared to men. However, weight-normalized clearance values are similar in women and men. No dosage adjustment is needed based on gender (see PRECAUTIONS, Use in Women).

Renal Impairment

In patients with severe renal impairment, pharmacokinetic parameters for pantoprazole were similar to those of healthy subjects. No dosage adjustment is necessary in patients with renal impairment or in patients undergoing hemodialysis.

Hepatic Impairment

In patients with mild to severe hepatic impairment, maximum pantoprazole concentrations increased only slightly (1.5-fold) relative to healthy subjects. Although serum half-life values increased to 7-9 hours and AUC values increased by 5- to 7-fold in hepatic-impaired patients, these increases were no greater than those observed in slow CYP2C19 metabolizers, where no dosage frequency adjustment is warranted. These pharmacokinetic changes in hepatic-impaired patients result in minimal drug accumulation following once daily multiple-dose administration. No dosage adjustment is needed in patients with mild to severe hepatic impairment. Doses higher than 40 mg/day have not been studied in hepatically-impaired patients.

Drug-Drug Interactions

Pantoprazole is metabolized mainly by CYP2C19 and to minor extents by CYPs 3A4, 2D6, and 2C9. In in vivo drug-drug interaction studies with CYP2C19 substrates (diazepam [also a CYP3A4 substrate] and phenytoin [also a CYP3A4 inducer]), nifedipine, midazolam, and clarithromycin (CYP3A4 substrates), metoprolol (a CYP2D6 substrate), diclofenac, naproxen and piroxicam (CYP2C9 substrates), and theophylline (a CYP1A2 substrate) in healthy subjects, the pharmacokinetics of pantoprazole were not significantly altered. It is, therefore, expected that other drugs metabolized by CYPs 2C19, 3A4, 2D6, 2C9, and 1A2 would not significantly affect the pharmacokinetics of pantoprazole. In vivo studies also suggest that pantoprazole does not significantly affect the kinetics of other drugs (cisapride, theophylline, diazepam [and its active metabolite, desmethyldiazepam], phenytoin, warfarin, metoprolol, nifedipine, carbamazepine, midazolam, clarithromycin, naproxen, piroxicam, and oral contraceptives [levonorgestrel/ethinyl estradiol]) metabolized by CYPs 2C19, 3A4, 2C9, 2D6, and 1A2. Therefore, it is expected that pantoprazole would not significantly affect the pharmacokinetics of other drugs metabolized by these isozymes. Dosage adjustment of such drugs is not necessary when they are coadministered with pantoprazole. In other in vivo studies, digoxin, ethanol, glyburide, antipyrine, caffeine, metronidazole, and amoxicillin had no clinically relevant interactions with pantoprazole. Although no significant drug-drug interactions have been observed in clinical studies, the potential for significant drug-drug interactions with more than once daily dosing with high doses of pantoprazole has not been studied in poor metabolizers or individuals who are hepatically impaired.

Pharmacodynamics

Mechanism of Action

Pantoprazole is a proton pump inhibitor (PPI) that suppresses the final step in gastric acid production by covalently binding to the (H^+,K^+)-ATPase enzyme system at the secretory surface of the gastric parietal cell. This effect leads to inhibition of both basal and stimulated gastric acid secretion irrespective of the stimulus. The binding to the (H^+,K^+)-ATPase results in a duration of antisecretory effect that persists longer than 24 hours for all doses tested.

Antisecretory Activity

Under maximal acid stimulatory conditions using pentagastrin, a dose-dependent decrease in gastric acid output occurs after a single dose of oral (20-80 mg) or a single dose of intravenous (20-120 mg) pantoprazole in healthy volunteers. Pantoprazole given once daily results in increasing inhibition of gastric acid secretion. Following the initial oral dose of 40 mg pantoprazole, a 51% mean inhibition was achieved by 2.5 hours. With once a day dosing for 7 days the mean inhibition was increased to 85%. Pantoprazole suppressed acid secretion in excess of 95% in half of the subjects. Acid secretion had returned to normal within a week after the last dose of pantoprazole; there was no evidence of rebound hypersecretion.

In a series of dose-response studies pantoprazole, at oral doses ranging from 20 to 120 mg, caused dose-related increases in median basal gastric pH and in the percent of time gastric pH was > 3 and > 4. Treatment with 40 mg of pantoprazole produced optimal increases in gastric pH which were significantly greater than the 20-mg dose. Doses higher than 40 mg (60, 80, 120 mg) did not result in further significant increases in median gastric pH. The effects of pantoprazole on median pH from one double-blind crossover study are shown below.

Effect of Single Daily Doses of Oral Pantoprazole on Intragastric pH
 | –––––––—––––––––Median pH on day 7—–––––––––––––
Time | Placebo | 20 mg | 40 mg | 80 mg
8 a.m. - 8 a.m. (24 hours) | 1.3 | 2.9* | 3.8*# | 3.9*#
8 a.m. - 10 p.m. (Daytime) | 1.6 | 3.2* | 4.4*# | 4.8*#
10 p.m. - 8 a.m. (Nighttime) | 1.2 | 2.1* | 3.0* | 2.6*
* Significantly different from placebo
# Significantly different from 20 mg

Serum Gastrin Effects

Fasting serum gastrin levels were assessed in two double-blind studies of the acute healing of erosive esophagitis (EE) in which 682 patients with gastroesophageal reflux disease (GERD) received 10, 20, or 40 mg of pantoprazole sodium for up to 8 weeks. At 4 weeks of treatment there was an increase in mean gastrin levels of 7%, 35%, and 72% over pretreatment values in the 10, 20, and 40 mg treatment groups, respectively. A similar increase in serum gastrin levels was noted at the 8 week visit with mean increases of 3%, 26%, and 84% for the three pantoprazole dose groups. Median serum gastrin levels remained within normal limits during maintenance therapy with pantoprazole sodium delayed-release tablets.

In long-term international studies involving over 800 patients, a 2- to 3-fold mean increase from the pretreatment fasting serum gastrin level was observed in the initial months of treatment with pantoprazole at doses of 40 mg per day during GERD maintenance studies and 40 mg or higher per day in patients with refractory GERD. Fasting serum gastrin levels generally remained at approximately 2 to 3 times baseline for up to 4 years of periodic follow-up in clinical trials.

Following healing of gastric or duodenal ulcers with pantoprazole treatment, elevated gastrin levels return to normal by at least 3 months.

Enterochromaffin-Like (ECL) Cell Effects

In 39 patients treated with oral pantoprazole 40 mg to 240 mg daily (majority receiving 40 mg to 80 mg) for up to 5 years, there was a moderate increase in ECL-cell density starting after the first year of use which appeared to plateau after 4 years.

In a nonclinical study in Sprague-Dawley rats, lifetime exposure (24 months) to pantoprazole at doses of 0.5 to 200 mg/kg/day resulted in dose-related increases in gastric ECL-cell proliferation and gastric neuroendocrine (NE)-cell tumors. Gastric NE-cell tumors in rats may result from chronic elevation of serum gastrin concentrations. The high density of ECL cells in the rat stomach makes this species highly susceptible to the proliferative effects of elevated gastrin concentrations produced by proton pump inhibitors. However, there were no observed elevations in serum gastrin following the administration of pantoprazole at a dose of 0.5 mg/kg/day. In a separate study, a gastric NE-cell tumor without concomitant ECL-cell proliferative changes was observed in 1 female rat following 12 months of dosing with pantoprazole at 5 mg/kg/day and a 9 month off-dose recovery (see PRECAUTIONS, Carcinogenesis, Mutagenesis, Impairment of Fertility).

Other Effects

No clinically relevant effects of pantoprazole on cardiovascular, respiratory, ophthalmic, or central nervous system function have been detected. In a clinical pharmacology study, pantoprazole 40 mg given once daily for 2 weeks had no effect on the levels of the following hormones: cortisol, testosterone, triiodothyronine (T3), thyroxine (T4), thyroid-stimulating hormone (TSH), thyronine-binding protein, parathyroid hormone, insulin, glucagon, renin, aldosterone, follicle-stimulating hormone, luteinizing hormone, prolactin, and growth hormone.

In a 1-year study of GERD patients treated with pantoprazole 40 mg or 20 mg, there were no changes from baseline in overall levels of T3, T4, and TSH.

Clinical Studies

Pantoprazole sodium delayed-release tablets were used in all clinical trials.

Erosive Esophagitis (EE) Associated with Gastroesophageal Reflux Disease (GERD)

A U.S. multicenter double-blind, placebo-controlled study of pantoprazole sodium 10 mg, 20 mg, or 40 mg once daily was conducted in 603 patients with reflux symptoms and endoscopically diagnosed EE of grade 2 or above (Hetzel-Dent scale). In this study, approximately 25% of enrolled patients had severe EE of grade 3 and 10% had grade 4. The percentages of patients healed (per protocol, n = 541) in this study were as follows:

Erosive Esophagitis Healing Rates (per protocol)
–––––––––––Pantoprazole sodium––––––––––– |  |  |  | Placebo
Week | 10 mg QD (n = 153) | 20 mg QD (n = 158) | 40 mg QD (n = 162) | (n = 68)
4 | 45.6%^+ | 58.4%^+# | 75.0%^+* | 14.3%
8 | 66.0%^+ | 83.5 %^+# | 92.6%^+* | 39.7%
^+ (p < 0.001) pantoprazole sodium versus placebo.
* (p < 0.05) versus 10 mg, or 20 mg pantoprazole sodium.
# (p < 0.05) versus 10 mg pantoprazole sodium.

In this study, all pantoprazole sodium treatment groups had significantly greater healing rates than the placebo group. This was true regardless of H. pylori status for the 40-mg and 20-mg pantoprazole sodium treatment groups. The 40-mg dose of pantoprazole sodium resulted in healing rates significantly greater than those found with either the 20- or 10-mg dose.

A significantly greater proportion of patients taking pantoprazole sodium 40 mg experienced complete relief of daytime and nighttime heartburn and the absence of regurgitation starting from the first day of treatment compared with placebo. Patients taking pantoprazole sodium consumed significantly fewer antacid tablets per day than those taking placebo.

Pantoprazole sodium 40 mg and 20 mg once daily were also compared with nizatidine 150 mg twice daily in a U.S. multicenter, double-blind study of 243 patients with reflux symptoms and endoscopically diagnosed EE of grade 2 or above. The percentages of patients healed (per protocol, n = 212) were as follows:

Erosive Esophagitis Healing Rates (per protocol)
–––––––Pantoprazole sodium––––––– |  |  | Nizatidine
Week | 20 mg QD (n = 72) | 40 mg QD (n = 70) | 150 mg BID (n = 70)
4 | 61.4%^+ | 64.0%^+ | 22.2%
8 | 79.2%^+ | 82.9%^+ | 41.4%
^+ (p < 0.001) pantoprazole sodium versus nizatidine.

Once daily treatment with pantoprazole sodium 40 mg or 20 mg resulted in significantly superior rates of healing at both 4 and 8 weeks compared with twice daily treatment with 150 mg of nizatidine. For the 40 mg treatment group, significantly greater healing rates compared to nizatidine were achieved regardless of the H. pylori status.

A significantly greater proportion of the patients in the pantoprazole sodium treatment groups experienced complete relief of nighttime heartburn and regurgitation starting on the first day and of daytime heartburn on the second day compared with those taking nizatidine 150 mg twice daily. Patients taking pantoprazole sodium consumed significantly fewer antacid tablets per day than those taking nizatidine.

Long-Term Maintenance of Healing of Erosive Esophagitis

Two independent, multicenter, randomized, double-blind, comparator-controlled trials of identical design were conducted in GERD patients with endoscopically-confirmed healed erosive esophagitis to demonstrate efficacy of pantoprazole sodium in long-term maintenance of healing. The two U.S. studies enrolled 386 and 404 patients, respectively, to receive either 10 mg, 20 mg, or 40 mg of pantoprazole sodium delayed-release tablets once daily or 150 mg of ranitidine twice daily. As demonstrated in the table below, pantoprazole sodium 40 mg and 20 mg were significantly superior to ranitidine at every time point with respect to the maintenance of healing. In addition, pantoprazole sodium 40 mg was superior to all other treatments studied.

Long-Term Maintenance of Healing of Erosive Gastroesophageal Reflux Disease (GERD Maintenance): Percentage of Patients Who Remained Healed
 | Pantoprazole sodium 20 mg QD | Pantoprazole sodium 40 mg QD | Ranitidine 150 mg BID
Study 1 | n = 75 | n = 74 | n = 75
Month 1 Month 3 Month 6 Month 12 | 91* 82* 76* 70* | 99* 93*# 90*# 86*# | 68 54 44 35
Study 2 | n = 74 | n = 88 | n = 84
Month 1 Month 3 Month 6 Month 12 | 89* 78* 72* 72* | 92*# 91*# 88*# 83* | 62 47 39 37
* (p < 0.05 vs ranitidine)
# (p < 0.05 vs. pantoprazole sodium 20 mg)
Note: Pantoprazole sodium 10 mg was superior (p < 0.05) to ranitidine in study 2 but not study 1.

Pantoprazole sodium 40 mg was superior to ranitidine in reducing the number of daytime and nighttime heartburn episodes from the first through the twelfth month of treatment. Pantoprazole sodium 20 mg, administered once daily, was also effective in reducing episodes of daytime and nighttime heartburn in one trial.

Number of Episodes of Heartburn (mean ± SD)
 |  | Pantoprazole sodium 40 mg QD | Ranitidine 150 mg BID
Month 1 | Daytime Nighttime | 5.1 ± 1.6* 3.9 ± 1.1* | 18.3 ± 1.6 11.9 ± 1.1
Month 12 | Daytime Nighttime | 2.9 ± 1.5* 2.5 ± 1.2* | 17.5 ± 1.5 13.8 ± 1.3
* (p < 0.001 vs ranitidine, combined data from the 2 U.S. studies)

Pathological Hypersecretory Conditions Including Zollinger-Ellison Syndrome

In a multicenter, open-label trial of 35 patients with pathological hypersecretory conditions, such as Zollinger-Ellison syndrome with or without multiple endocrine neoplasia-type I, pantoprazole sodium successfully controlled gastric acid secretion. Doses ranging from 80 mg daily to 240 mg daily maintained gastric acid output below 10 mEq/h in patients without prior acid-reducing surgery and below 5 mEq/h in patients with prior acid-reducing surgery.

Doses were initially titrated to the individual patient needs, and adjusted in some patients based on the clinical response with time (see DOSAGE AND ADMINISTRATION). Pantoprazole sodium was well tolerated at these dose levels for prolonged periods (greater than 2 years in some patients).

INDICATIONS AND USAGE

Short-Term Treatment of Erosive Esophagitis Associated With Gastroesophageal Reflux Disease (GERD)

Pantoprazole sodium delayed-release tablets are indicated for the short-term treatment (up to 8 weeks) in the healing and symptomatic relief of erosive esophagitis. For those patients who have not healed after 8 weeks of treatment, an additional 8-week course of pantoprazole sodium may be considered.

Maintenance of Healing of Erosive Esophagitis

Pantoprazole sodium delayed-release tablets are indicated for maintenance of healing of erosive esophagitis and reduction in relapse rates of daytime and nighttime heartburn symptoms in patients with gastroesophageal reflux disease (GERD). Controlled studies did not extend beyond 12 months.

Pathological Hypersecretory Conditions Including Zollinger-Ellison Syndrome

Pantoprazole sodium delayed-release tablets are indicated for the long-term treatment of pathological hypersecretory conditions, including Zollinger-Ellison syndrome.

CONTRAINDICATIONS

Pantoprazole sodium delayed-release tablets are contraindicated in patients with known hypersensitivity to any component of the formulation.

PRECAUTIONS

General

Symptomatic response to therapy with pantoprazole does not preclude the presence of gastric malignancy.

Owing to the chronic nature of erosive esophagitis, there may be a potential for prolonged administration of pantoprazole. In long-term rodent studies, pantoprazole was carcinogenic and caused rare types of gastrointestinal tumors. The relevance of these findings to tumor development in humans is unknown.

Generally, daily treatment with any acid-suppressing medications over a long period of time (eg, longer than 3 years) may lead to malabsorption of cyanocobalamin (Vitamin B-12) caused by hypo- or achlorhydria. Rare reports of cyanocobalamin deficiency occurring with acid-suppressing therapy have been reported in the literature. This possibility should be considered if clinical symptoms consistent with cyanocobalamin deficiency are observed.

Atrophic gastritis has been noted occasionally in gastric corpus biopsies from patients treated long-term with pantoprazole, particularly in patients who were H. pylori positive.

Information for Patients

Patients should be cautioned that pantoprazole sodium delayed-release tablets SHOULD NOT BE SPLIT, CRUSHED OR CHEWED. The tablets should be swallowed whole, with or without food in the stomach. Concomitant administration of antacids does not affect the absorption of pantoprazole.

Drug Interactions

Pantoprazole is metabolized through the cytochrome P450 system, primarily the CYP2C19 and CYP3A4 isozymes, and subsequently undergoes Phase II conjugation (see CLINICAL PHARMACOLOGY, Drug-Drug Interactions).

Based on studies evaluating possible interactions of pantoprazole with other drugs, no dosage adjustment is needed with concomitant use of the following: theophylline, cisapride, antipyrine, caffeine, carbamazepine, diazepam (and its active metabolite, desmethyldiazepam), diclofenac, naproxen, piroxicam, digoxin, ethanol, glyburide, an oral contraceptive (levonorgestrel/ethinyl estradiol), metoprolol, nifedipine, phenytoin, warfarin (see below), midazolam, clarithromycin, metronidazole, or amoxicillin. Clinically relevant interactions of pantoprazole with other drugs with the same metabolic pathways are not expected. Therefore, when coadministered with pantoprazole, adjustment of the dosage of pantoprazole or of such drugs may not be necessary. There was also no interaction with concomitantly administered antacids. There have been postmarketing reports of increased INR and prothrombin time in patients receiving proton pump inhibitors, including pantoprazole, and warfarin concomitantly. Increases in INR and prothrombin time may lead to abnormal bleeding and even death. Patients treated with proton pump inhibitors and warfarin concomitantly should be monitored for increases in INR and prothrombin time.

Concomitant use of atazanavir and proton pump inhibitors is not recommended. Coadministration of atazanavir with proton pump inhibitors is expected to substantially decrease atazanavir plasma concentrations and thereby reduce its therapeutic effect.

Because of profound and long lasting inhibition of gastric acid secretion, pantoprazole may interfere with absorption of drugs where gastric pH is an important determinant of their bioavailability (eg, ketoconazole, ampicillin esters, and iron salts).

Carcinogenesis, Mutagenesis, Impairment of Fertility

In a 24-month carcinogenicity study, Sprague-Dawley rats were treated orally with doses of 0.5 to 200 mg/kg/day, about 0.1 to 40 times the exposure on a body surface area basis of a 50-kg person dosed at 40 mg/day. In the gastric fundus, treatment at 0.5 to 200 mg/kg/day produced enterochromaffin-like (ECL) cell hyperplasia and benign and malignant neuroendocrine cell tumors in a dose-related manner. In the forestomach, treatment at 50 and 200 mg/kg/day (about 10 and 40 times the recommended human dose on a body surface area basis) produced benign squamous cell papillomas and malignant squamous cell carcinomas. Rare gastrointestinal tumors associated with pantoprazole treatment included an adenocarcinoma of the duodenum at 50 mg/kg/day, and benign polyps and adenocarcinomas of the gastric fundus at 200 mg/kg/day. In the liver, treatment at 0.5 to 200 mg/kg/day produced dose-related increases in the incidences of hepatocellular adenomas and carcinomas. In the thyroid gland, treatment at 200 mg/kg/day produced increased incidences of follicular cell adenomas and carcinomas for both male and female rats.

Sporadic occurrences of hepatocellular adenomas and a hepatocellular carcinoma were observed in Sprague-Dawley rats exposed to pantoprazole in 6-month and 12-month toxicity studies.

In a 24-month carcinogenicity study, Fischer 344 rats were treated orally with doses of 5 to 50 mg/kg/day, approximately 1 to 10 times the recommended human dose based on body surface area. In the gastric fundus, treatment at 5 to 50 mg/kg/day produced enterochromaffin-like (ECL) cell hyperplasia and benign and malignant neuroendocrine cell tumors. Dose selection for this study may not have been adequate to comprehensively evaluate the carcinogenic potential of pantoprazole.

In a 24-month carcinogenicity study, B6C3F1 mice were treated orally with doses of 5 to 150 mg/kg/day, 0.5 to 15 times the recommended human dose based on body surface area. In the liver, treatment at 150 mg/kg/day produced increased incidences of hepatocellular adenomas and carcinomas in female mice. Treatment at 5 to 150 mg/kg/day also produced gastric fundic ECL cell hyperplasia.

A 26-week p53 +/- transgenic mouse carcinogenicity study was not positive.

Pantoprazole was positive in the in vitro human lymphocyte chromosomal aberration assays, in one of two mouse micronucleus tests for clastogenic effects, and in the in vitro Chinese hamster ovarian cell/HGPRT forward mutation assay for mutagenic effects. Equivocal results were observed in the in vivo rat liver DNA covalent binding assay. Pantoprazole was negative in the in vitro Ames mutation assay, the in vitro unscheduled DNA synthesis (UDS) assay with rat hepatocytes, the in vitro AS52/GPT mammalian cell-forward gene mutation assay, the in vitro thymidine kinase mutation test with mouse lymphoma L5178Y cells, and the in vivo rat bone marrow cell chromosomal aberration assay.

Pantoprazole at oral doses up to 500 mg/kg/day in male rats (98 times the recommended human dose based on body surface area) and 450 mg/kg/day in female rats (88 times the recommended human dose based on body surface area) was found to have no effect on fertility and reproductive performance.

Pregnancy

Teratogenic Effects

Pregnancy Category B

Teratology studies have been performed in rats at oral doses up to 450 mg/kg/day (88 times the recommended human dose based on body surface area) and rabbits at oral doses up to 40 mg/kg/day (16 times the recommended human dose based on body surface area) and have revealed no evidence of impaired fertility or harm to the fetus due to pantoprazole. There are, however, no adequate and well-controlled studies in pregnant women. Because animal reproduction studies are not always predictive of human response, this drug should be used during pregnancy only if clearly needed.

Nursing Mothers

Pantoprazole and its metabolites are excreted in the milk of rats. Pantoprazole excretion in human milk has been detected in a study of a single nursing mother after a single 40 mg oral dose. The clinical relevance of this finding is not known. Many drugs which are excreted in human milk have a potential for serious adverse reactions in nursing infants. Based on the potential for tumorigenicity shown for pantoprazole in rodent carcinogenicity studies, a decision should be made whether to discontinue nursing or to discontinue the drug, taking into account the benefit of the drug to the mother.

Pediatric Use

Safety and effectiveness in pediatric patients have not been established.

Use in Women

Erosive esophagitis healing rates in the 221 women treated with pantoprazole sodium delayed-release tablets in U.S. clinical trials were similar to those found in men. In the 122 women treated long-term with pantoprazole sodium 40 mg or 20 mg, healing was maintained at a rate similar to that in men. The incidence rates of adverse events were also similar for men and women.

Use in Elderly

In short-term U.S. clinical trials, erosive esophagitis healing rates in the 107 elderly patients (≥ 65 years old) treated with pantoprazole sodium were similar to those found in patients under the age of 65. The incidence rates of adverse events and laboratory abnormalities in patients aged 65 years and older were similar to those associated with patients younger than 65 years of age.

Laboratory Tests

There have been reports of false-positive urine screening tests for tetrahydrocannabinol (THC) in patients receiving most proton pump inhibitors, including pantoprazole. An alternative confirmatory method should be considered to verify positive results.

ADVERSE REACTIONS

Worldwide, more than 11,100 patients have been treated with pantoprazole in clinical trials involving various dosages and duration of treatment. In general, pantoprazole has been well tolerated in both short-term and long-term trials.

In two U.S. controlled clinical trials involving pantoprazole sodium 10, 20, or 40 mg doses for up to 8 weeks, there were no dose-related effects on the incidence of adverse events. The following adverse events considered by investigators to be possibly, probably, or definitely related to drug occurred in 1% or more in the individual studies of GERD patients on therapy with pantoprazole sodium.

Most Frequent Adverse Events Reported as Drug Related in Short-term Domestic Trials
 | ––––––––––––––––––––––% Incidence–––––––––––––––––
 | Study 300-US |  | Study 301-US
Study Event | Pantoprazole sodium (n = 521) | Placebo (n = 82) | Pantoprazole sodium (n = 161) | Nizatidine (n = 82)
Headache Diarrhea Flatulence Abdominal pain Rash Eructation Insomnia Hyperglycemia | 6 4 2 1 <1 1 <1 1 | 6 1 2 2 0 1 2 0 | 9 6 4 4 2 0 1 <1 | 13 6 0 4 0 0 1 0

Note: Only adverse events with an incidence greater than or equal to the comparators are shown.

In international short-term, double-blind or open-label clinical trials involving 20 mg to 80 mg per day, the following adverse events were reported to occur in 1% or more of 2805 GERD patients receiving pantoprazole for up to 8 weeks.

Adverse Events in GERD Patients in Short-term International Trials
 | –––––––––––––––––––––––––% Incidence–––––––––––––––––––
Study Event | Pantoprazole Total (N = 2805) | Ranitidine 300 mg (N = 594) | Omeprazole 20 mg (N = 474) | Famotidine 40 mg (N = 239)
Headache Diarrhea Abdominal pain | 2 2 1 | 3 2 1 | 2 2 <1 | 1 <1 <1

In two U.S. controlled clinical trials involving pantoprazole sodium 10, 20, or 40 mg doses for up to 12 months, the following adverse events considered by investigators to be possibly, probably, or definitely related to drug occurred in 1% or more of GERD patients on long-term therapy.

Most Frequent Adverse Events Reported as Drug Related in Long-term Domestic Trials
 | –––––––––––––––––––% Incidence–––––––––––––––
Study Event | Pantoprazole sodium (n = 536) | Ranitidine (n = 185)
Headache Abdominal pain Liver function tests abnormal Nausea Vomiting | 5 3 2 2 2 | 2 1 <1 2 2
Note: Only adverse events with an incidence greater than or equal to the comparators are shown.

In addition, in these short- and long-term domestic and international trials, the following treatment-emergent events, regardless of causality, occurred at a rate of ≥ 1% in pantoprazole-treated patients: anxiety, arthralgia, asthenia, back pain, bronchitis, chest pain, constipation, cough increased, dizziness, dyspepsia, dyspnea, flu syndrome, gastroenteritis, gastrointestinal disorder, hyperlipemia, hypertonia, infection, liver function tests abnormal, migraine, nausea, neck pain, pain, pharyngitis, rectal disorder, rhinitis, SGPT increased, sinusitis, upper respiratory tract infection, urinary frequency, urinary tract infection, and vomiting.

Additional treatment-emergent adverse experiences occurring in < 1% of pantoprazole-treated patients from these trials are listed below by body system. In most instances the relationship to pantoprazole was unclear.

BODY AS A WHOLE: abscess, allergic reaction, chills, cyst, face edema, fever, generalized edema, heat stroke, hernia, laboratory test abnormal, malaise, moniliasis, neoplasm, non-specified drug reaction, photosensitivity reaction.

CARDIOVASCULAR SYSTEM: abnormal electrocardiogram, angina pectoris, arrhythmia, atrial fibrillation/flutter, cardiovascular disorder, chest pain substernal, congestive heart failure, hemorrhage, hypertension, hypotension, myocardial infarction, myocardial ischemia, palpitation, retinal vascular disorder, syncope, tachycardia, thrombophlebitis, thrombosis, vasodilatation.

DIGESTIVE SYSTEM: anorexia, aphthous stomatitis, cardiospasm, colitis, dry mouth, duodenitis, dysphagia, enteritis, esophageal hemorrhage, esophagitis, gastrointestinal carcinoma, gastrointestinal hemorrhage, gastrointestinal moniliasis, gingivitis, glossitis, halitosis, hematemesis, increased appetite, melena, mouth ulceration, oral moniliasis, periodontal abscess, periodontitis, rectal hemorrhage, stomach ulcer, stomatitis, stools abnormal, tongue discoloration, ulcerative colitis.

ENDOCRINE SYSTEM: diabetes mellitus, glycosuria, goiter.

HEPATO-BILIARY SYSTEM: biliary pain, hyperbilirubinemia, cholecystitis, cholelithiasis, cholestatic jaundice, hepatitis, alkaline phosphatase increased, gamma glutamyl transpeptidase increased, SGOT increased.

HEMIC AND LYMPHATIC SYSTEM: anemia, ecchymosis, eosinophilia, hypochromic anemia, iron deficiency anemia, leukocytosis, leukopenia, thrombocytopenia.

METABOLIC AND NUTRITIONAL: dehydration, edema, gout, peripheral edema, thirst, weight gain, weight loss.

MUSCULOSKELETAL SYSTEM: arthritis, arthrosis, bone disorder, bone pain, bursitis, joint disorder, leg cramps, neck rigidity, myalgia, tenosynovitis.

NERVOUS SYSTEM: abnormal dreams, confusion, convulsion, depression, dry mouth, dysarthria, emotional lability, hallucinations, hyperkinesia, hypesthesia, libido decreased, nervousness, neuralgia, neuritis, neuropathy, paresthesia, reflexes decreased, sleep disorder, somnolence, thinking abnormal, tremor, vertigo.

RESPIRATORY SYSTEM: asthma, epistaxis, hiccup, laryngitis, lung disorder, pneumonia, voice alteration.

SKIN AND APPENDAGES: acne, alopecia, contact dermatitis, dry skin, eczema, fungal dermatitis, hemorrhage, herpes simplex, herpes zoster, lichenoid dermatitis, maculopapular rash, pruritus, skin disorder, skin ulcer, sweating, urticaria.

SPECIAL SENSES: abnormal vision, amblyopia, cataract specified, deafness, diplopia, ear pain, extraocular palsy, glaucoma, otitis externa, taste perversion, tinnitus.

UROGENITAL SYSTEM: albuminuria, balanitis, breast pain, cystitis, dysmenorrhea, dysuria, epididymitis, hematuria, impotence, kidney calculus, kidney pain, nocturia, prostatic disorder, pyelonephritis, scrotal edema, urethral pain, urethritis, urinary tract disorder, urination impaired, vaginitis.

In an open-label US clinical trial conducted in 35 patients with pathological hypersecretory conditions treated with pantoprazole sodium for up to 27 months, the adverse events reported were consistent with the safety profile of the drug in other populations.

Postmarketing Reports

There have been spontaneous reports of adverse events with the postmarketing use of pantoprazole. These reports include the following:

BODY AS A WHOLE: anaphylaxis (including anaphylactic shock), angioedema (Quincke's edema).

DIGESTIVE SYSTEM: increased salivation, nausea, pancreatitis.

HEMIC AND LYMPHATIC SYSTEM: pancytopenia.

HEPATO-BILIARY SYSTEM: hepatocellular damage leading to jaundice and hepatic failure.

MUSCULOSKELETAL SYSTEM: elevated CPK (creatine phosphokinase), rhabdomyolysis.

NERVOUS SYSTEM: confusion, hypokinesia, speech disorder, vertigo.

SKIN AND APPENDAGES: severe dermatologic reactions, including erythema multiforme, Stevens-Johnson syndrome, and toxic epidermal necrolysis (TEN, some fatal).

SPECIAL SENSES: anterior ischemic optic neuropathy, blurred vision, tinnitus.

UROGENITAL SYSTEM: interstitial nephritis.

Laboratory Values

In two U.S. controlled, short-term trials in patients with erosive esophagitis associated with GERD, 0.4% of the patients on pantoprazole sodium 40 mg experienced SGPT elevations of greater than three times the upper limit of normal at the final treatment visit. In two U.S. controlled, long-term trials in patients with erosive esophagitis associated with GERD, none of 178 patients (0%) on pantoprazole sodium 40 mg and two of 181 patients (1.1%) on pantoprazole sodium 20 mg experienced significant transaminase elevations at 12 months (or earlier if a patient discontinued prematurely). Significant elevations of SGOT or SGPT were defined as values at least three times the upper limit of normal that were non-sporadic and had no clear alternative explanation. The following changes in laboratory parameters were reported as adverse events: creatinine increased, hypercholesterolemia, and hyperuricemia.

OVERDOSAGE

Experience in patients taking very high doses of pantoprazole is limited. There have been spontaneous reports of overdosage with pantoprazole, including a suicide in which pantoprazole 560 mg and undetermined amounts of chloroquine and zopiclone were also ingested. There have also been spontaneous reports of patients taking similar amounts of pantoprazole (400 mg and 600 mg) with no adverse effects.

Pantoprazole is not removed by hemodialysis. In case of overdosage, treatment should be symptomatic and supportive.

Single oral doses of pantoprazole at 709 mg/kg, 798 mg/kg, and 887 mg/kg were lethal to mice, rats, and dogs, respectively. The symptoms of acute toxicity were hypoactivity, ataxia, hunched sitting, limb-splay, lateral position, segregation, absence of ear reflex, and tremor.

DOSAGE AND ADMINISTRATION

Treatment of Erosive Esophagitis

The recommended adult oral dose is 40 mg given once daily for up to 8 weeks. For those patients who have not healed after 8 weeks of treatment, an additional 8-week course of pantoprazole sodium may be considered (see INDICATIONS AND USAGE).

Maintenance of Healing of Erosive Esophagitis

The recommended adult oral dose is one pantoprazole sodium 40 mg delayed-release tablet, taken daily (see CLINICAL PHARMACOLOGY, Clinical Studies).

Pathological Hypersecretory Conditions Including Zollinger-Ellison Syndrome

The dosage of pantoprazole sodium in patients with pathological hypersecretory conditions varies with the individual patient. The recommended adult starting dose is 40 mg twice daily. Dosage regimens should be adjusted to individual patient needs and should continue for as long as clinically indicated. Doses up to 240 mg daily have been administered. Some patients have been treated continuously with pantoprazole sodium for more than 2 years.

No dosage adjustment is necessary in patients with renal impairment, hepatic impairment, or for elderly patients. Doses higher than 40 mg/day have not been studied in hepatically-impaired patients. No dosage adjustment is necessary in patients undergoing hemodialysis.

Pantoprazole sodium delayed-release tablets should be swallowed whole, with or without food in the stomach. If patients are unable to swallow a 40 mg tablet, two 20 mg tablets may be taken. Concomitant administration of antacids does not affect the absorption of pantoprazole sodium.

Patients should be cautioned that pantoprazole sodium delayed-release tablets should not be split, chewed or crushed.

HOW SUPPLIED

Pantoprazole sodium delayed-release tablets are supplied as 40 mg yellow oval biconvex delayed‑release tablets imprinted with PROTONIX (brown ink) on one side.

They are available as follows:

- NDC 67046-535-30 blister of 30

Storage

Store pantoprazole sodium delayed-release tablets at 20°-25°C (68°-77°F); excursions permitted to 15°-30°C (59°-86°F). [See USP Controlled Room Temperature.]

United States Patent Numbers: 4,758,579; 5,997,903.

Marketed by

esiLederle

Division of Wyeth

Philadelphia, PA 19101

under license from

Nycomed GmbH

D78467 Konstanz, Germany

W10525C006

ET02

Rev 11/08

Repackaged by:
Contract Pharmacy Services-PA
125 Titus Ave Suite 200
Warrington, PA 18976 USA

Original--02/2010--NJW

PACKAGE LABEL – PRINCIPAL DISPLAY PANEL – 40 MG LABEL

esiLEDERLE™ NDC 67046-535-30

Pantoprazole Sodium

Delayed-Release Tablets

Equivalent to 40 mg pantoprazole

40 mg

Rx Only

30 Tablets